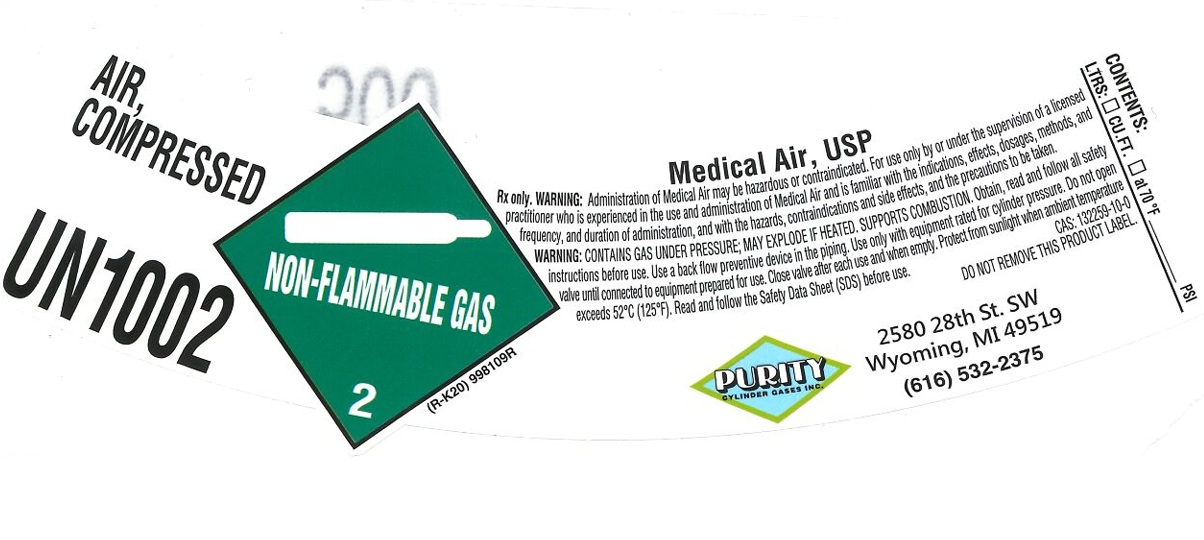 DRUG LABEL: AIR
NDC: 10927-104 | Form: GAS
Manufacturer: PURITY CYLINDER GASES INC
Category: prescription | Type: HUMAN PRESCRIPTION DRUG LABEL
Date: 20251201

ACTIVE INGREDIENTS: AIR 99 L/100 L

AIR

PACKAGE LABEL

AIR, COMPRESSED

UN1002

Medical Air, USP

Rx only. WARNING: Administration of Medical Air may be hazardous or contraindicated. For use only by or under the supervision of a licensed practitioner who is experienced in the use and administration of Medical Air and is familiar with the indications, effects, dosages, methods, and frequency, and duration of administration, and with the hazards, contraindications and side effects, and the precautions to be taken.

WARNING: CONTAINS GAS UNDER PRESSURE; MAY EXPLODE IF HEATED. SUPPORTS COMBUSTION. Obtain, read and follow all safety instructions before use. Use a back flow preventive device in the piping. Use only with equipment rated for cylinder pressure. Do not open valve until connected to equipment prepared for use. Close valve after each use and when empty. Protect from sunlight when ambient temperature exceeds 52 C (125 F). Read and follow the Safety Data Sheet (SDS) before use.

CAS: 132259-10-0

DO NOT REMOVE THIS PRODUCT LABEL.

PURITY CYLINDER GASES INC.

2580 28th St. SW

Wyoming, MI 49519

(616) 532-2375

CONTENTS:

LTRS: CU.FT. at 70 F PSI